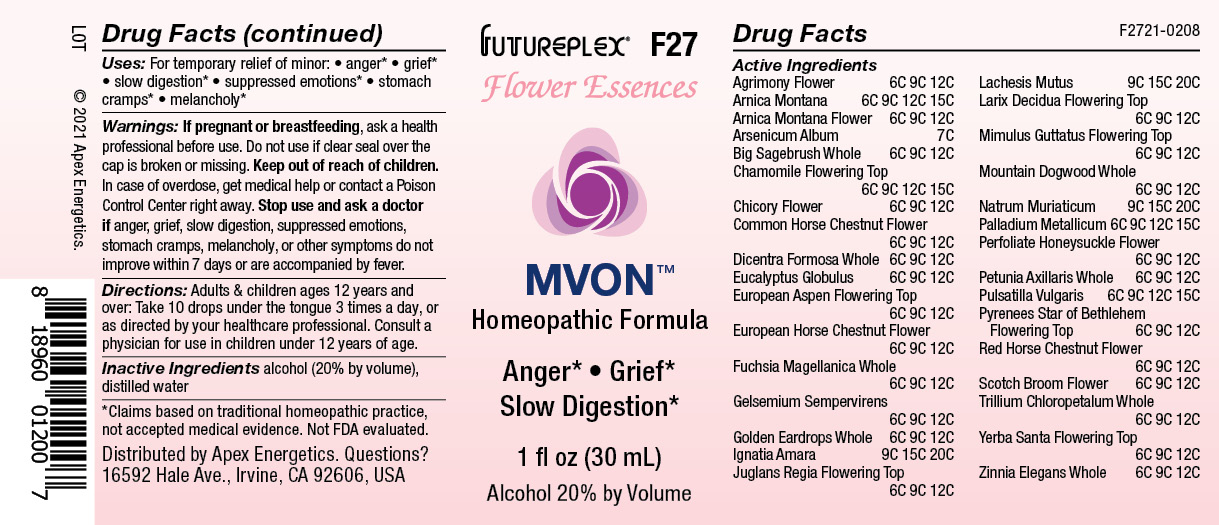 DRUG LABEL: F27
NDC: 63479-0627 | Form: SOLUTION/ DROPS
Manufacturer: Apex Energetics Inc.
Category: homeopathic | Type: HUMAN OTC DRUG LABEL
Date: 20240108

ACTIVE INGREDIENTS: CICHORIUM INTYBUS FLOWER 12 [hp_C]/1 mL; AESCULUS HIPPOCASTANUM FLOWER 12 [hp_C]/1 mL; PALLADIUM 15 [hp_C]/1 mL; PULSATILLA VULGARIS 15 [hp_C]/1 mL; ORNITHOGALUM UMBELLATUM FLOWERING TOP 12 [hp_C]/1 mL; JUGLANS REGIA FLOWERING TOP 12 [hp_C]/1 mL; STRYCHNOS IGNATII SEED 20 [hp_C]/1 mL; LACHESIS MUTA VENOM 20 [hp_C]/1 mL; GELSEMIUM SEMPERVIRENS ROOT 12 [hp_C]/1 mL; AGRIMONIA EUPATORIA FLOWER 12 [hp_C]/1 mL; EUCALYPTUS GLOBULUS LEAF 12 [hp_C]/1 mL; MIMULUS GUTTATUS FLOWERING TOP 12 [hp_C]/1 mL; PETUNIA AXILLARIS WHOLE 12 [hp_C]/1 mL; TRILLIUM CHLOROPETALUM WHOLE 12 [hp_C]/1 mL; ZINNIA ELEGANS WHOLE 12 [hp_C]/1 mL; ARSENIC TRIOXIDE 7 [hp_C]/1 mL; SODIUM CHLORIDE 20 [hp_C]/1 mL; ARNICA MONTANA 15 [hp_C]/1 mL; ARNICA MONTANA FLOWER 12 [hp_C]/1 mL; DICENTRA FORMOSA WHOLE 12 [hp_C]/1 mL; POPULUS TREMULA FLOWERING TOP 12 [hp_C]/1 mL; FUCHSIA MAGELLANICA WHOLE 12 [hp_C]/1 mL; CYTISUS SCOPARIUS FLOWER 12 [hp_C]/1 mL; ARTEMISIA TRIDENTATA WHOLE 12 [hp_C]/1 mL; MATRICARIA CHAMOMILLA FLOWERING TOP 15 [hp_C]/1 mL; EHRENDORFERIA CHRYSANTHA WHOLE 12 [hp_C]/1 mL; LARIX DECIDUA FLOWERING TOP 12 [hp_C]/1 mL; CORNUS NUTTALLII WHOLE 12 [hp_C]/1 mL; LONICERA CAPRIFOLIUM FLOWER 12 [hp_C]/1 mL; AESCULUS CARNEA FLOWER 12 [hp_C]/1 mL; ERIODICTYON CALIFORNICUM FLOWERING TOP 12 [hp_C]/1 mL
INACTIVE INGREDIENTS: WATER; ALCOHOL

F27

Active Ingredients
Agrimony Flower | 6C 9C 12C
Arnica Montana | 6C 9C 12C 15C
Arnica Montana Flower | 6C 9C 12C
Arsenicum Album | 7C
Big Sagebrush Whole | 6C 9C 12C
Chamomile Flowering Top | 6C 9C 12C 15C
Chicory Flower | 6C 9C 12C
Common Horse Chestnut Flower | 6C 9C 12C
Dicentra Formosa Whole | 6C 9C 12C
Eucalyptus Globulus | 6C 9C 12C
European Aspen Flowering Top | 6C 9C 12C
European Horse Chestnut Flower | 6C 9C 12C
Fuchsia Magellanica Whole | 6C 9C 12C
Gelsemium Sempervirens | 6C 9C 12C
Golden Eardrops Whole | 6C 9C 12C
Ignatia Amara | 9C 15C 20C
Juglans Regia Flowering Top | 6C 9C 12C
Lachesis Mutus | 9C 15C 20C
Larix Decidua Flowering Top | 6C 9C 12C
Mimulus Guttatus Flowering Top | 6C 9C 12C
Mountain Dogwood Whole | 6C 9C 12C
Natrum Muriaticum | 9C 15C 20C
Palladium Metallicum | 6C 9C 12C 15C
Perfoliate Honeysuckle Flower | 6C 9C 12C
Petunia Axillaris Whole | 6C 9C 12C
Pulsatilla Vulgaris | 6C 9C 12C 15C
Pyrenees Star Of Bethlehem Flowering Top | 6C 9C 12C
Red Horse-Chestnut Flower | 6C 9C 12C
Scotch Broom Flower | 6C 9C 12C
Trillium Chloropetalum Whole | 6C 9C 12C
Yerba Santa Flowering Top | 6C 9C 12C
Zinnia Elegans Whole | 6C 9C 12C

INDICATIONS AND USAGE

Uses:

For temporary relief of minor:

anger*

grief*

slow digestion*

suppressed emotions*

stomach cramps*

melancholy*

*Claims based on traditional homeopathic practice, not accepted medical evidence. Not FDA evaluated.

WARNINGS

PREGNANCY OR BREAST FEEDING

If pregnant or breastfeeding, ask a health professional before use.

Do not use if clear seal over the cap is broken or missing.

Keep out of reach of children. In case of overdose, get medical help or contact a Poison Control Center right away.

Stop use and ask a doctor if anger, grief, slow digestion, suppressed emotions, stomach cramps, melancholy, or other symptoms do not improve within 7 days or are accompanied by fever.

Directions:

Adults & children ages 12 years and over: Take 10 drops under the tongue 3 times a day, or as directed by your healthcare professional. Consult a physician for use in children under 12 years of age.

Inactive Ingredients

alcohol (20% by volume), distilled water

Distributed by Apex Energetics. Questions?

16592 Hale Ave., Irvine, CA 92606, USA

PACKAGE LABEL

FUTUREPLEX® F27

FLOWER ESSENCES

MVON™

Homeopathic Formula

Anger* Grief*

Slow Digestion*

1 fl oz (30 mL)

Alcohol 20% by Volume